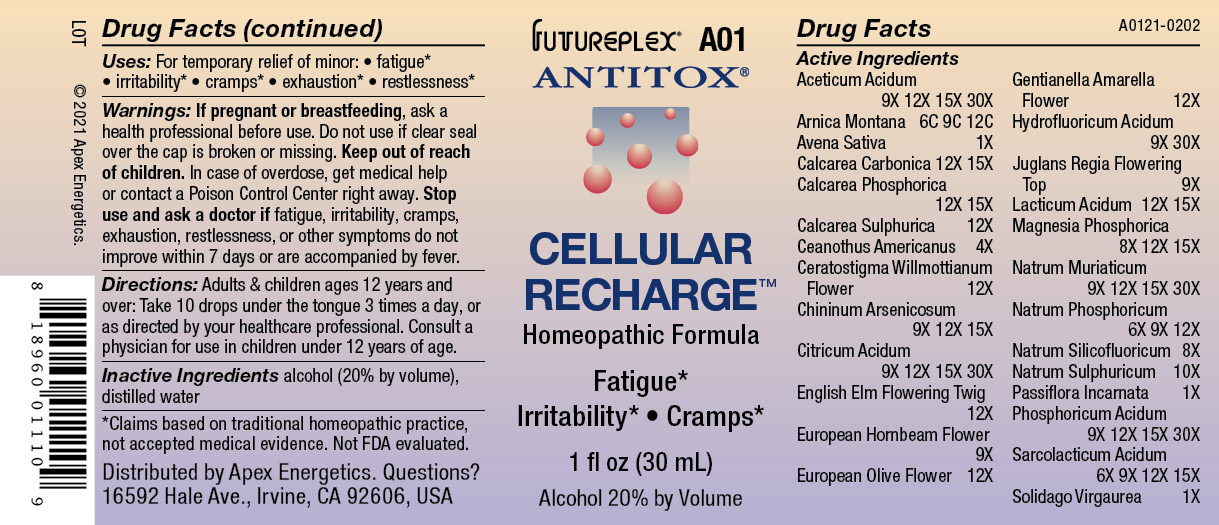 DRUG LABEL: A01
NDC: 63479-0101 | Form: SOLUTION/ DROPS
Manufacturer: Apex Energetics Inc.
Category: homeopathic | Type: HUMAN OTC DRUG LABEL
Date: 20240108

ACTIVE INGREDIENTS: CALCIUM SULFATE ANHYDROUS 12 [hp_X]/1 mL; CERATOSTIGMA WILLMOTTIANUM FLOWER 12 [hp_X]/1 mL; LACTIC ACID, L- 15 [hp_X]/1 mL; ARNICA MONTANA 12 [hp_C]/1 mL; OYSTER SHELL CALCIUM CARBONATE, CRUDE 15 [hp_X]/1 mL; ANHYDROUS CITRIC ACID 30 [hp_X]/1 mL; OLEA EUROPAEA FLOWER 12 [hp_X]/1 mL; GENTIANELLA AMARELLA FLOWER 12 [hp_X]/1 mL; ULMUS PROCERA FLOWERING TWIG 12 [hp_X]/1 mL; SODIUM PHOSPHATE, DIBASIC, HEPTAHYDRATE 12 [hp_X]/1 mL; PHOSPHORIC ACID 30 [hp_X]/1 mL; CARPINUS BETULUS FLOWER 9 [hp_X]/1 mL; SOLIDAGO VIRGAUREA FLOWERING TOP 1 [hp_X]/1 mL; ACETIC ACID 30 [hp_X]/1 mL; AVENA SATIVA FLOWERING TOP 1 [hp_X]/1 mL; SODIUM CHLORIDE 30 [hp_X]/1 mL; TRIBASIC CALCIUM PHOSPHATE 15 [hp_X]/1 mL; CEANOTHUS AMERICANUS LEAF 4 [hp_X]/1 mL; SODIUM HEXAFLUOROSILICATE 8 [hp_X]/1 mL; QUININE ARSENITE 15 [hp_X]/1 mL; HYDROFLUORIC ACID 30 [hp_X]/1 mL; JUGLANS REGIA FLOWERING TOP 9 [hp_X]/1 mL; MAGNESIUM PHOSPHATE, DIBASIC TRIHYDRATE 15 [hp_X]/1 mL; SODIUM SULFATE 10 [hp_X]/1 mL; PASSIFLORA INCARNATA FLOWERING TOP 1 [hp_X]/1 mL; LACTIC ACID, DL- 15 [hp_X]/1 mL
INACTIVE INGREDIENTS: WATER; ALCOHOL

A01

Active Ingredients
Aceticum Acidum | 9X 12X 15X 30X
Arnica Montana | 6C 9C 12C
Avena Sativa | 1X
Calcarea Carbonica | 12X 15X
Calcarea Phosphorica | 12X 15X
Calcarea Sulphurica | 12X
Ceanothus Americanus | 4X
Ceratostigma Willmottianum Flower | 12X
Chininum Arsenicosum | 9X 12X 15X
Citricum Acidum | 9X 12X 15X 30X
English Elm Flowering Twig | 12X
European Hornbeam Flower | 9X
European Olive Flower | 12X
Gentianella Amarella Flower | 12X
Hydrofluoricum Acidum | 9X 30X
Juglans Regia Flowering Top | 9X
Lacticum Acidum | 12X 15X
Magnesia Phosphorica | 8X 12X 15X
Natrum Muriaticum | 9X 12X 15X 30X
Natrum Phosphoricum | 6X 9X 12X
Natrum Silicofluoricum | 8X
Natrum Sulphuricum | 10X
Passiflora Incarnata | 1X
Phosphoricum Acidum | 9X 12X 15X 30X
Sarcolacticum Acidum | 6X 9X 12X 15X
Solidago Virgaurea | 1X

INDICATIONS AND USAGE

Uses:

For temporary relief of minor:

fatigue*

irritability*

cramps*

exhaustion*

restlessness*

*Claims based on traditional homeopathic practice, not accepted medical evidence. Not FDA evaluated.

Warnings:

PREGNANCY OR BREAST FEEDING

If pregnant or breastfeeding, ask a health professional before use.

Do not use if clear seal over the cap is broken or missing.

Keep out of reach of children. In case of overdose, get medical help or contact a Poison Control Center right away.

Stop use and ask a doctor if fatigue, irritability, cramps, exhaustion, restlessness, or other symptoms do not improve within 7 days or are accompanied by fever.

Directions:

Adults & children ages 12 years and over: Take 10 drops under the tongue 3 times a day, or as directed by your healthcare professional. Consult a physician for use in children under 12 years of age.

Inactive Ingredients

alcohol (20% by volume), distilled water

Distributed by Apex Energetics. Questions?
16592 Hale Ave., Irvine, CA 92606, USA

PACKAGE LABEL

FUTUREPLEX® A01

ANTITOX®

CELLULAR RECHARGE™

Homeopathic Formula

Fatigue*

Irritability*

Cramps*

1 fl oz (30 mL)

Alcohol 20% by Volume